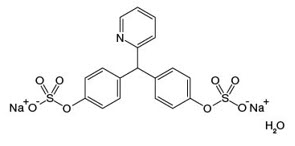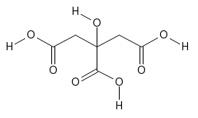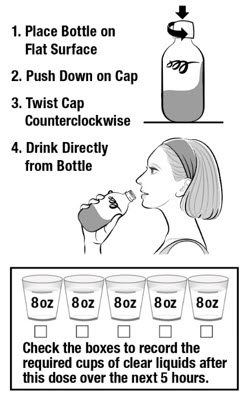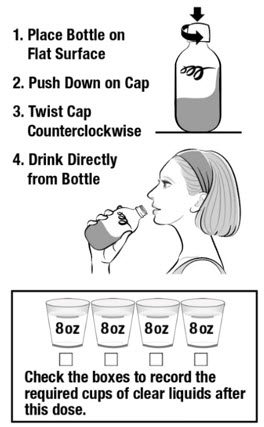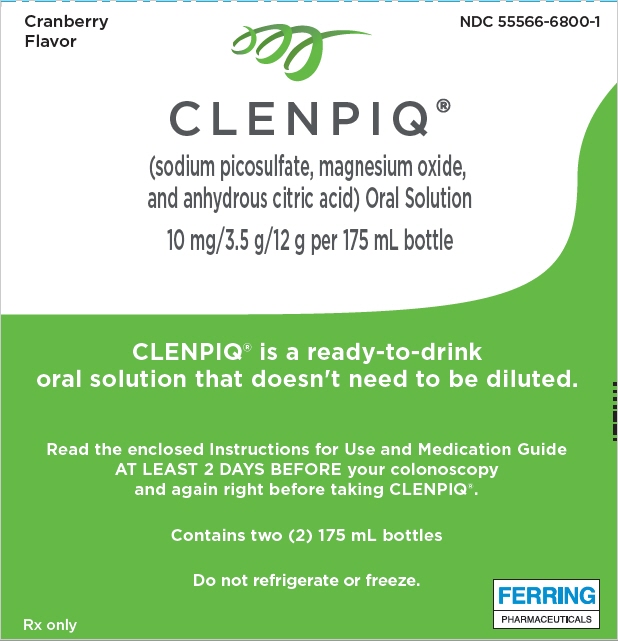 DRUG LABEL: CLENPIQ
NDC: 55566-6800 | Form: LIQUID
Manufacturer: Ferring Pharmaceuticals Inc.
Category: prescription | Type: HUMAN PRESCRIPTION DRUG LABEL
Date: 20250404

ACTIVE INGREDIENTS: SODIUM PICOSULFATE 10 mg/175 mL; MAGNESIUM OXIDE 3.5 g/175 mL; ANHYDROUS CITRIC ACID 12 g/175 mL
INACTIVE INGREDIENTS: EDETATE DISODIUM; SODIUM BENZOATE; CRANBERRY; MALIC ACID; SUCRALOSE; ACESULFAME POTASSIUM; SODIUM HYDROXIDE; SODIUM METABISULFITE; WATER

HIGHLIGHTS OF PRESCRIBING INFORMATION

These highlights do not include all the information needed to use CLENPIQ® safely and effectively. See full prescribing information for CLENPIQ.
CLENPIQ® (sodium picosulfate, magnesium oxide, and anhydrous citric acid) oral solution
Initial U.S. Approval: 2012

1 INDICATIONS AND USAGE

CLENPIQ® is a combination of sodium picosulfate, a stimulant laxative, and magnesium oxide and anhydrous citric acid, which form magnesium citrate, an osmotic laxative, indicated for cleansing of the colon as a preparation for colonoscopy in adults and pediatric patients ages 9 years and older. (1)

2 DOSAGE AND ADMINISTRATION

Administration:

- CLENPIQ is ready to drink. It does not need to be diluted prior to administration. One bottle of CLENPIQ is equivalent to one dose. (2.1)
- Two doses of CLENPIQ are required for a complete preparation for colonoscopy as a Split-Dose regimen. (2.1)
- Consume five or more 8-ounce cups of clear liquids after the first dose and four or more 8-ounce cups of clear liquids after the second dose. (2.2)
- Consume a variety of clear liquids after each dose of CLENPIQ. Ensure inclusion of balanced electrolyte solution along with other clear liquids. (2.1, 5.1, 5.5)
- Administer oral medications at least 1 hour before starting CLENPIQ. (2.1, 7.2)
- If taking tetracycline or fluoroquinolone antibiotics, iron, digoxin, chlorpromazine, or penicillamine, take these medications at least 2 hours before and not less than 6 hours after administration of CLENPIQ. (2.1, 7.3)
- For complete information on preparation before colonoscopy and administration of the dosage regimen, see full prescribing information. (2.1, 2.2)

Split-Dose Dosage Regimen (2.2)

- First dose: administer during evening before the colonoscopy
- Second dose: administer the next day, during the morning prior to the colonoscopy.

3 DOSAGE FORMS AND STRENGTHS

CLENPIQ oral solution: Each bottle contains 10 mg of sodium picosulfate, 3.5 g of magnesium oxide, and 12 g of anhydrous citric acid in 175 mL of solution (3)

4 CONTRAINDICATIONS

- Severe renal impairment (creatinine clearance less than 30 mL/minute) (4, 5.3, 8.6)
- Gastrointestinal (GI) obstruction or ileus (4)
- Bowel perforation (4)
- Toxic colitis or toxic megacolon (4)
- Gastric retention (4)
- Hypersensitivity to any of the ingredients in CLENPIQ (4)

5 WARNINGS AND PRECAUTIONS

- Risk of fluid and electrolyte abnormalities, arrhythmia, seizures, and renal impairment: Encourage adequate hydration, assess concurrent medications, and consider laboratory assessments prior to and after use. (5.1, 5.2, 5.3, 5.4, 7.1)
- Use in patients with renal impairment or taking concomitant medications that affect renal function: Use caution, ensure adequate hydration, and consider testing. (4, 5.3, 7.1)
- Syncope: Resulted in serious outcomes including falls, head injuries, and fractures; encourage adequate hydration. (5.5)
- Mucosal ulcerations: Consider potential for mucosal ulcerations when interpreting colonoscopy findings in patients with known or suspected inflammatory bowel disease. (5.6)
- Suspected GI obstruction or perforation: Rule out diagnosis before administration. (4, 5.7)
- Patients at risk for aspiration: Observe during administration. (5.8)

6 ADVERSE REACTIONS

Most common adverse reactions are:

- Adults (≥2%): nausea, headache, hypermagnesemia, abdominal pain and dehydration or dizziness. (6.1)
- Pediatrics 9 to 16 years (>5%): nausea, vomiting, and abdominal pain. (6.1)

To report SUSPECTED ADVERSE REACTIONS, contact Ferring Pharmaceuticals Inc. at 1-888-FERRING (1-888-337-7464) or FDA at 1-800-FDA-1088 or www.fda.gov/medwatch.

7 DRUG INTERACTIONS

Drugs that increase risks due to fluid and electrolyte changes. (7.1)

FULL PRESCRIBING INFORMATION

1 INDICATIONS AND USAGE

CLENPIQ is indicated for cleansing of the colon as a preparation for colonoscopy in adults and pediatric patients 9 years of age and older.

2 DOSAGE AND ADMINISTRATION

2.1 Important Administration Instructions

- Correct fluid and electrolyte abnormalities before administration of CLENPIQ [see Warnings and Precautions (5.1)].
- CLENPIQ is ready to drink. It is a clear solution with possible presence of visible particles and it does not need to be diluted prior to administration. One bottle of CLENPIQ is equivalent to one dose.
- Two doses of CLENPIQ are required for a complete preparation for colonoscopy as a Split-Dose regimen.
- The Split-Dose method consists of two separate doses: the first dose during the evening before the colonoscopy and the second dose the next day, during the morning prior to the colonoscopy [see Dosage and Administration (2.2)].
- Consume five or more 8-ounce cups of clear liquids after the first dose and four or more 8-ounce cups of clear liquids after the second dose [see Dosage and Administration (2.2)].
- Consume a variety of clear liquids. Clear liquids should include balanced electrolyte solution [see Warnings and Precautions (5.1, 5.5)]. Additional clear liquids, other than water, include black coffee or tea, plain jello, clear broth or bouillon, clear juices without pulp, ginger ale and other sodas, and frozen juice bars. Do not drink anything colored red or purple.
- Consume only clear liquids (no solid food) on the day before colonoscopy and until after the colonoscopy.
- Do not eat solid food or dairy and do not drink anything colored red or purple.
- Do not drink alcohol.
- Stop consumption of all liquids at least 2 hours before the colonoscopy.
- Do not take other laxatives while taking CLENPIQ.
- Administer oral medications at least one hour before starting each dose of CLENPIQ.
- If taking tetracycline or fluoroquinolone antibiotics, iron, digoxin, chlorpromazine, or penicillamine, take these medications at least 2 hours before and not less than 6 hours after administration of CLENPIQ.

2.2 Split-Dose Dosage Regimen

The recommended dosage in adults and pediatric patients 9 years of age and older is shown below. Instruct patients to take two separate doses in conjunction with liquids, as follows:

Dose 1 – On the day before colonoscopy:

- Instruct patients to consume only clear liquids (no solid food or dairy) on the day before the colonoscopy up until 2 hours before the time of the colonoscopy.
- Take the first dose (1 bottle) of CLENPIQ during the evening before the colonoscopy (e.g., 5:00 PM to 9:00 PM).
- Consume at least five 8-ounce cups (cup provided) of clear liquids after the CLENPIQ dose over the next 5 hours.
- If severe bloating, distention, or abdominal pain occurs, following the first dose, delay the second dose until the symptoms resolve.

Dose 2 – Next morning on the day of colonoscopy (start approximately 5 hours prior to colonoscopy):

- Continue to consume only clear liquids (no solid food or dairy).
- Take the second dose (the second bottle) of CLENPIQ.
- Consume four or more 8-ounce cups (cup provided) of clear liquids after the CLENPIQ dose and up to 2 hours before the colonoscopy.

3 DOSAGE FORMS AND STRENGTHS

Oral solution: Each bottle contains 10 mg of sodium picosulfate, 3.5 grams of magnesium oxide, and 12 grams of anhydrous citric acid in 175 mL of colorless to slightly yellow, clear solution with possible presence of visible particles.

4 CONTRAINDICATIONS

CLENPIQ is contraindicated in the following conditions:

- Patients with severe renal impairment (creatinine clearance less than 30 mL/minute), which may result in accumulation of magnesium [see Warnings and Precautions (5.3)].
- Gastrointestinal obstruction or ileus [see Warnings and Precautions (5.6)].
- Bowel perforation [see Warnings and Precautions (5.6)].
- Toxic colitis or toxic megacolon.
- Gastric retention.
- Hypersensitivity to any of the ingredients in CLENPIQ [see Adverse Reactions (6.2)].

5 WARNINGS AND PRECAUTIONS

5.1 Serious Fluid and Electrolyte Abnormalities

Advise patients to hydrate adequately before, during, and after the use of CLENPIQ. Use caution in patients with congestive heart failure when replacing fluids. If a patient develops significant vomiting or signs of dehydration including signs of orthostatic hypotension after taking CLENPIQ, consider performing post-colonoscopy lab tests (electrolytes, creatinine, and BUN) and treat accordingly. Approximately 20% of patients in both arms (sodium picosulfate, magnesium oxide, and anhydrous citric acid, or 2 L of PEG + E plus two × 5-mg bisacodyl tablets) of clinical trials of another oral sodium picosulfate, magnesium oxide, and anhydrous citric acid product had orthostatic changes in blood pressure and/or heart rate on the day of colonoscopy and up to seven days post colonoscopy. In a single study of patients 9 to 16 years of age, approximately 20% of patients who received another oral product of sodium picosulfate, magnesium oxide, and anhydrous citric acid had orthostatic changes (changes in blood pressure and/or heart rate) compared with approximately 7% of those who received the comparator (PEG) [see Clinical Studies (14)]. These changes occurred up to five days post colonoscopy.

Fluid and electrolyte disturbances can lead to serious adverse reactions including cardiac arrhythmias, seizures, renal impairment, and syncope [see Warnings and Precautions (5.5)]. Correct fluid and electrolyte abnormalities before treatment with CLENPIQ. Advise patients to consume a variety of clear liquids (e.g., balanced electrolyte solution), and not only water after each dose of CLENPIQ. In addition, use caution when prescribing CLENPIQ for patients who have conditions or who are using medications that increase the risk for fluid and electrolyte disturbances or that may increase the risk of seizure, arrhythmia, and renal impairment [see Drug Interactions (7.1)].

5.2 Seizures

There have been reports of generalized tonic-clonic seizures and/or loss of consciousness with the use of bowel preparation products in patients with no prior history of seizures. The seizure cases were associated with electrolyte abnormalities (e.g., hyponatremia, hypokalemia, hypocalcemia, and hypomagnesemia) and low serum osmolality. The neurologic abnormalities resolved with correction of fluid and electrolyte abnormalities.

Use caution when prescribing CLENPIQ for patients with a history of seizures and in patients at risk of seizure, such as patients taking medications that lower the seizure threshold (e.g., tricyclic antidepressants), patients withdrawing from alcohol or benzodiazepines, patients with known or suspected hyponatremia [see Adverse Reactions (6.2)].

5.3 Use in Patients with Renal Impairment

CLENPIQ is contraindicated in patients with severe renal impairment (creatinine clearance less than 30 mL/min), accumulation of magnesium in plasma may occur. Use caution when prescribing CLENPIQ for patients with mild to moderate renal impairment or patients taking concomitant medications that may affect renal function (such as diuretics, angiotensin-converting enzyme inhibitors, angiotensin receptor blockers, or non-steroidal anti-inflammatory drugs) [see Drug Interactions (7.1)]. These patients may be at increased risk for renal injury. Advise these patients of the importance of adequate hydration before, during, and after the use of CLENPIQ. Consider performing baseline and post-colonoscopy laboratory tests (electrolytes, creatinine, and BUN) in these patients.

5.4 Cardiac Arrhythmias

There have been rare reports of serious arrhythmias associated with the use of ionic osmotic laxative products for bowel preparation. Use caution when prescribing CLENPIQ for patients at increased risk of arrhythmias (e.g., patients with a history of prolonged QT, uncontrolled arrhythmias, recent myocardial infarction, unstable angina, congestive heart failure, or cardiomyopathy). Consider pre-dose and post-colonoscopy ECGs in patients at increased risk of serious cardiac arrhythmias.

5.5 Syncope

Syncope has been reported with CLENPIQ in the postmarketing setting. Some cases were serious events that included falls with associated head injuries or fractures requiring hospitalization. In some cases, electrolyte abnormalities were also present (e.g., hyponatremia and hypokalemia). Cases have been reported after one or two CLENPIQ doses and many of these cases occurred within 12 hours of dosing. Patients should be aware of the risk of syncope during treatment and adequately hydrate before, during, and after the use of CLENPIQ. Advise patients to consume a variety of clear liquids (e.g., balanced electrolyte solution), not only water after each dose of CLENPIQ and to get up gradually from a lying or sitting position [see Warnings and Precautions (5.1)].

5.6 Colonic Mucosal Ulceration, Ischemic Colitis, and Ulcerative Colitis

Osmotic laxatives may produce colonic mucosal aphthous ulcerations and there have been reports of more serious cases of ischemic colitis requiring hospitalization. Concurrent use of additional stimulant laxatives with CLENPIQ may increase this risk. Consider the potential for mucosal ulcerations when interpreting colonoscopy findings in patients with known or suspected inflammatory bowel disease [see Adverse Reactions (6.2)].

5.7 Use in Patients with Significant Gastrointestinal Disease

If gastrointestinal obstruction or perforation is suspected, perform appropriate diagnostic studies to rule out these conditions before administering CLENPIQ [see Contraindications (4)]. Use with caution in patients with severe active ulcerative colitis.

5.8 Aspiration

Patients with impaired gag reflex are at risk for regurgitation or aspiration during the administration of CLENPIQ. Observe these patients during the administration of CLENPIQ.

6 ADVERSE REACTIONS

The following serious or otherwise important adverse reactions for bowel preparations are described elsewhere in the labeling:

- Serious Fluid and Electrolyte Abnormalities [see Warnings and Precautions (5.1)]
- Seizures [see Warnings and Precautions (5.2)]
- Use in Patients with Renal Impairment [see Warnings and Precautions (5.3)]
- Cardiac Arrhythmias [see Warnings and Precautions (5.4)]
- Syncope [see Warnings and Precautions (5.5)]
- Colonic Mucosal Ulceration, Ischemic Colitis and Ulcerative Colitis [see Warnings and Precautions (5.6)]
- Use in Patients with Significant Gastrointestinal Disease [see Warnings and Precautions (5.7)]
- Aspiration [see Warnings and Precautions (5.8)]

6.1 Clinical Trials Experience

Because clinical trials are conducted under widely varying conditions, adverse reaction rates observed in the clinical trials of a drug cannot be directly compared to rates in clinical trials of another drug and may not reflect the rates observed in practice.

Adults

Clinical Study of CLENPIQ - Study 1

Table 1 displays the most common adverse reactions in a randomized, multicenter, assessor-blinded, non-inferiority trial of CLENPIQ for colon cleansing in adults (Study 1). CLENPIQ was compared to another oral sodium picosulfate, magnesium oxide, and anhydrous citric acid product, both administered according to the Split-Dose dosage regimen [see Clinical Studies (14)].

Table 1: Common Adverse Reactions Observed in at Least 2% of Patients Undergoing Colon Cleansing in Study 1
Adverse Reaction | Split-Dose Regimen
Adverse Reaction | CLENPIQ (N=448) % | Sodium picosulfate, magnesium oxide, and anhydrous citric acid [Powder for reconstitution] (N=453) %
Nausea | 3 | 3
Headache | 3 | 3
Hypermagnesemia [Magnesium levels returned to normal within one week after colonoscopy in all patients in the CLENPIQ group.] | 2 | 5
Abdominal pain [Abdominal pain included reports of abdominal pain, abdominal pain upper, and abdominal pain lower.] | 2 | 2
Dehydration or dizziness | 2 | 2

Clinical Study of Another Sodium Picosulfate, Magnesium Oxide and Anhydrous Citric Acid Product - Study 2

In a randomized, multicenter, investigator-blinded, active-controlled clinical trial for colon cleansing in adults, another oral sodium picosulfate, magnesium oxide, and anhydrous citric acid product was compared with a regimen of two liters (2 L) of polyethylene glycol plus electrolytes solution (PEG + E) and two 5-mg bisacodyl tablets (Study 2). In this study the protocol specified that abdominal bloating, distention, pain/cramping, and watery diarrhea, which are known to occur in response to bowel preparation, were documented as adverse events only if they required medical intervention (such as a change in study drug or led to discontinuation, therapeutic or diagnostic procedures, met the criteria for serious adverse event) or showed clinically significant worsening during the study that was not in the frame of the usual clinical course, as determined by the investigator. The most common adverse reactions in Study 2 are shown in Table 2.

Table 2: Common Adverse Reactions [abdominal bloating, distention, pain/cramping, and watery diarrhea not requiring an intervention were not collected] Observed in at Least 1% of Patients Undergoing Colon Cleansing in Study 2
Adverse Reaction | Split-Dose Regimen
Adverse Reaction | Sodium picosulfate, magnesium oxide, and anhydrous citric acid (N=305) % | 2 L PEG + E [2 L PEG + E = two liters polyethylene glycol plus electrolytes solution] with 2 × 5-mg bisacodyl tablets (N=298) %
Nausea | 3 | 4
Headache | 2 | 2
Vomiting | 1 | 3

Electrolyte Abnormalities

In Study 1, rates of abnormal electrolyte shifts were generally similar between CLENPIQ and another sodium picosulfate, magnesium oxide, and anhydrous citric acid product (Table 3). In general, these shifts were transient and not clinically significant.

In Study 2, sodium picosulfate, magnesium oxide, and anhydrous citric acid was in general associated with numerically higher rates of abnormal electrolyte shifts on the day of colonoscopy compared to the control regimen (Table 3). These shifts were transient in nature and numerically similar between treatment arms at the Day 28 visit.

Table 3: Shifts from Normal Baseline to Outside the Normal Range Post-Baseline
Laboratory Parameter (direction of change) | Visit | Split-Dose Regimen Study 1 |  | Split-Dose Regimen Study 2
Laboratory Parameter (direction of change) | Visit | CLENPIQ | Sodium picosulfate, magnesium oxide, and anhydrous citric acid [Powder for reconstitution] | Sodium picosulfate, magnesium oxide, and anhydrous citric acid | 2 L PEG+E with 2 × 5 mg bisacodyl tablets
 |  | n/N (%) |  | n/N (%)
Potassium (low) | Day of Colonoscopy | 34/422 (8.1) | 10/423 (2.4) | 19/260 (7.3) | 11/268 (4.1)
 | 24-48 hours | 13/417 (3.1) | 3/423 (0.7) | 3/302 (1.0) | 2/294 (0.7)
 | Day 7 | 7/420 (1.7) | 6/425 (1.4) | 11/285 (3.9) | 8/279 (2.9)
 | Day 28 | 3/421 (0.7) | 7/423 (1.7) | 11/284 (3.9) | 8/278 (2.9)
Sodium (low) | Day of Colonoscopy | 4/426 (0.9) | 23/443 (5.2) | 11/298 (3.7) | 3/295 (1.0)
 | 24-48 hours | 6/423 (1.4) | 9/441 (2.0) | 1/303 (0.3) | 1/295 (0.3)
 | Day 7 | 6/423 (1.4) | 9/440 (2.0) | 2/300 (0.7) | 1/292 (0.3)
 | Day 28 | 8/427 (1.9) | 9/439 (2.1) | 2/299 (0.7) | 3/291 (1.0)
Chloride (low) | Day of Colonoscopy | 23/437 (5.3) | 16/444 (3.6) | 11/301 (3.7) | 1/298 (0.3)
 | 24-48 hours | 3/434 (0.7) | 3/442 (0.7) | 1/303 (0.3) | 0/295 (0.0)
 | Day 7 | 3/434 (0.7) | 2/441 (0.5) | 1/303 (0.3) | 3/295 (1.0)
 | Day 28 | 4/438 (0.9) | 1/440 (0.2) | 2/302 (0.7) | 3/294 (1.0)
Magnesium (high) | Day of Colonoscopy | 112/431 (26.0) | 143/440 (32.5) | 34/294 (11.6) | 0/294 (0.0)
 | 24-48 hours | 23/427 (5.4) | 21/440 (4.8) | 0/303 (0.0) | 0/295 (0.0)
 | Day 7 | 11/428 (2.6) | 9/440 (2.0) | 0/297 (0.0) | 1/291 (0.3)
 | Day 28 | 10/432 (2.3) | 12/438 (2.7) | 1/296 (0.3) | 2/290 (0.7)
Calcium (low) | Day of Colonoscopy | 8/436 (1.8) | 1/446 (0.2) | 2/292 (0.7) | 1/286 (0.3)
 | 24-48 hours | 1/434 (0.2) | 0/444 (0.0) | 0/303 (0.0) | 0/295 (0.0)
 | Day 7 | 0/434 (0.0) | 0/444 (0.0) | 0/293 (0.0) | 1/283 (0.4)
 | Day 28 | 0/439 (0.0) | 2/442 (0.5) | 0/292 (0.0) | 1/282 (0.4)
Bicarbonate (low) | Day of Colonoscopy | 6/431 (1.4) | 35/438 (8.0) | N/A [Bicarbonate was not analyzed in Study 2.] | N/A
 | 24-48 hours | 40/430 (9.3) | 43/434 (9.9) | N/A | N/A
 | Day 7 | 37/430 (8.6) | 40/438 (9.1) | N/A | N/A
 | Day 28 | 33/433 (7.6) | 43/436 (9.9) | N/A | N/A
Creatinine (high) | Day of Colonoscopy | 6/427 (1.4) | 1/432 (0.2) | 5/260 (1.9) | 13/268 (4.9)
 | 24-48 hours | 6/425 (1.4) | 5/431 (1.2) | 1/303 (0.3) | 0/295 (0.0)
 | Day 7 | 5/426 (1.2) | 4/431 (0.9) | 10/264 (0.4) | 13/267 (4.8)
 | Day 28 | 4/429 (0.9) | 6/429 (1.4) | 11/264 (4.2) | 14/265(5.3)
N/A: not applicable.

Pediatrics

In the pediatric patients aged 9 to 16 years who received another oral product of sodium picosulfate, magnesium oxide, and anhydrous citric acid, the most common adverse reactions (> 5%) were nausea, vomiting, and abdominal pain [see Clinical Studies (14)]. Electrolytes abnormalities were observed in pediatric patients similar to those seen in adults. Three patients had abnormally low glucose levels (40 to 47 mg/dL). Two patients received sodium picosulfate, magnesium oxide, and anhydrous citric acid and one received the comparator (PEG). The abnormal values occurred at the colonoscopy visit for one patient (sodium picosulfate, magnesium oxide, and anhydrous citric acid) and at the 5-day follow up visit for the other two patients (sodium picosulfate, magnesium oxide, and anhydrous citric acid and PEG). All three patients were asymptomatic.

6.2 Postmarketing Experience

The following adverse reactions have been identified during post approval use of oral sodium picosulfate, magnesium oxide, and anhydrous citric acid products. Because these reactions are reported voluntarily from a population of uncertain size, it is not always possible to reliably estimate their frequency or establish a causal relationship to drug exposure.

Hypersensitivity: rash, urticaria, and purpura

Gastrointestinal: abdominal pain, diarrhea, fecal incontinence, proctalgia, vomiting, reversible aphthoid ileal ulcers, and ischemic colitis [see Warnings and Precautions (5.5)]

Neurologic: generalized tonic-clonic seizures with and without hyponatremia in epileptic patients, and syncope [see Warnings and Precautions (5.2, 5.5)].

7 DRUG INTERACTIONS

7.1 Drugs That May Increase Risks of Fluid and Electrolyte Abnormalities

Use caution when prescribing CLENPIQ for patients with conditions or who are taking other drugs, that increase the risk for fluid and electrolyte disturbances or may increase the risk of renal impairment, seizures, syncope, arrhythmias or QT prolongation in the setting of fluid and electrolyte abnormalities [see Warnings and Precautions (5.1, 5.2, 5.3, 5.4, 5.5)].

7.2 Potential for Reduced Drug Absorption

CLENPIQ can reduce the absorption of other co-administered drugs [see Dosage and Administration (2.1)]:

- Administer oral medications at least one hour before of the start of administration of CLENPIQ.
- Administer tetracycline and fluoroquinolone antibiotics [see Drug Interactions (7.3)], iron, digoxin, chlorpromazine, and penicillamine at least 2 hours before and not less than 6 hours after administration of CLENPIQ to avoid chelation with magnesium.

7.3 Antibiotics

Prior or concomitant use of antibiotics with CLENPIQ may reduce efficacy of CLENPIQ as conversion of sodium picosulfate to its active metabolite BHPM is mediated by colonic bacteria.

8 USE IN SPECIFIC POPULATIONS

8.1 Pregnancy

Risk Summary

There are no data with CLENPIQ use in pregnant women to determine a drug-associated risk of adverse developmental outcomes. In animal reproduction studies, no adverse developmental effects were observed in pregnant rats when sodium picosulfate, magnesium oxide, and anhydrous citric acid were administered orally at doses 1.2 times the recommended human dose based on body surface area during organogenesis.

The estimated background risk of major birth defects and miscarriage for the indicated population is unknown. All pregnancies have a background risk of birth defect, loss, or other adverse outcomes. In the U.S. general population, the estimated background risk of major birth defects and miscarriage in clinically recognized pregnancies is 2 to 4% and 15 to 20%, respectively.

Data

Animal Data

Reproduction studies with sodium picosulfate, magnesium oxide, and anhydrous citric acid have been performed in pregnant rats following oral administration of up to 2000 mg/kg twice daily (about 1.2 times the recommended human dose based on body surface area) during the period of organogenesis. There was no evidence of harm to the fetus due to sodium picosulfate, magnesium oxide, and anhydrous citric acid. The reproduction study in rabbits was not adequate, as treatment-related mortalities were observed at all doses. A pre and postnatal development study with sodium picosulfate, magnesium oxide, and anhydrous citric acid in rats showed no evidence of any adverse effect on pre and postnatal development at oral doses up to 2000 mg/kg twice daily (about 1.2 times the recommended human dose based on body surface area).

Published reproduction studies with sodium picosulfate in pregnant rats and rabbits during the period of organogenesis did not show evidence of harm to the fetus at doses up to 100 mg/kg (approximately 49 and 98 times, respectively, the recommended human dose of 10 mg sodium picosulfate based on body surface area).

8.2 Lactation

Risk Summary

There are no data on the presence of magnesium oxide or anhydrous citric acid in either human or animal milk, the effects on the breastfed infant, or the effects on milk production. Published data on lactating women indicate that the active metabolite of sodium picosulfate, bis-(p-hydroxyphenyl)-pyridyl-2-methane (BHPM) remained below the limit of detection (1 ng/mL) in breast milk after both single and multiple doses of 10 mg/day. There are no data on the effects of sodium picosulfate on the breastfed infant or on milk production. The developmental and health benefits of breastfeeding should be considered along with the mother's clinical need for CLENPIQ and any potential adverse effects on the breastfed infant from CLENPIQ or the underlying maternal condition.

8.4 Pediatric Use

The safety and effectiveness of CLENPIQ have been established for cleansing of the colon as a preparation for colonoscopy in pediatric patients 9 years of age and older. Use of CLENPIQ in this age group is supported by evidence from adequate and well-controlled trials in adults and a single, dose-ranging, controlled trial in 78 pediatric patients 9 to 16 years of age all of which evaluated another oral product of sodium picosulfate, magnesium oxide, and anhydrous citric acid [see Clinical Studies (14)]. The safety profile in this pediatric population was similar to that seen in adults [see Adverse Reactions (6.1)]. Monitor for possible hypoglycemia in pediatric patients, as CLENPIQ has no caloric substrate.

The safety and effectiveness of CLENPIQ in pediatric patients less than 9 years of age have not been established.

8.5 Geriatric Use

Of the 448 adult patients in Study 1 who received CLENPIQ, 124 (28%) patients were 65 years of age or older. No overall differences in safety or effectiveness were observed between geriatric patients and younger patients, and other reported clinical experience has not identified differences in responses between elderly and younger patients. Elderly patients are more likely to have decreased hepatic, renal, or cardiac function and may be more susceptible to adverse reactions resulting from fluid and electrolyte abnormalities [see Warnings and Precautions (5.1)].

8.6 Renal Impairment

CLENPIQ is contraindicated in patients with severe renal impairment (creatinine clearance less than 30 mL/min), as accumulation of magnesium in plasma may occur [see Contraindications (4)]. Patients with less severe renal impairment or patients taking concomitant medications that may affect renal function may be at increased risk for renal injury [see Warnings and Precautions (5.3)]. Advise these patients of the importance of adequate hydration before, during, and after the use of CLENPIQ [see Dosage and Administration (2.1)]. Consider performing baseline and post-colonoscopy laboratory tests (electrolytes, creatinine, and BUN) in these patients.

10 OVERDOSAGE

Overdosage of more than the recommended dose of CLENPIQ may lead to severe electrolyte disturbances, as well as dehydration and hypovolemia, with signs and symptoms of these disturbances [see Warnings and Precautions (5.1)]. Monitor for fluid and electrolyte disturbances and treat symptomatically.

11 DESCRIPTION

CLENPIQ (sodium picosulfate, magnesium oxide, and anhydrous citric acid) oral solution is a stimulant and osmotic laxative that is provided as a cranberry-flavored, colorless to slightly yellow, clear solution with possible presence of visible particles. CLENPIQ is supplied as two bottles in each carton.

Each bottle of CLENPIQ contains 10 mg sodium picosulfate, USP; 3.5 g magnesium oxide, USP; and 12 g anhydrous citric acid, USP. The product also contains the following inactive ingredients:

acesulfame potassium, cranberry flavor, disodium edetate, malic acid, sodium benzoate, sodium hydroxide, sodium metabisulfite, sucralose, and water. The cranberry flavor contains glyceryl triacetate (triacetin), maltodextrin, and sodium octenyl succinated starch.

The following is a description of the three active ingredients contained in CLENPIQ:

Sodium picosulfate is a stimulant laxative.

Sodium Picosulfate

- Chemical name: 4,4´-(2-pyridylmethylene) diphenyl bis(hydrogen sulfate) disodium salt, monohydrate
- Chemical formula: C18H13NNa2O8S2∙H2O
- Molecular weight: 499.4
- Structural formula:
  Sodium picosulfate

Magnesium citrate, which is formed in solution by the combination of magnesium oxide and anhydrous citric acid, is an osmotic laxative.

Magnesium Oxide

- Chemical name: Magnesium oxide
- Chemical formula: Mg O
- Molecular weight: 40.3
- Structural formula: Mg O

Anhydrous Citric Acid

- Chemical name: 2-hydroxypropane-1,2,3-tricarboxylic acid
- Chemical formula: C6H8O7
- Molecular weight: 192.1
- Structural formula:
  Anhydrous citric acid

12 CLINICAL PHARMACOLOGY

12.1 Mechanism of Action

Sodium picosulfate is hydrolyzed by colonic bacteria to form an active metabolite: bis-(p-hydroxy-phenyl)-pyridyl-2-methane, BHPM, which acts directly on the colonic mucosa to stimulate colonic peristalsis. Magnesium oxide and citric acid react to create magnesium citrate in solution, which is an osmotic agent that causes water to be retained within the gastrointestinal tract.

12.2 Pharmacodynamics

The stimulant laxative activity of sodium picosulfate together with the osmotic laxative activity of magnesium citrate produces a purgative effect which, when ingested with additional liquids, produces watery diarrhea.

12.3 Pharmacokinetics

Absorption

After administration of the first dose of another oral sodium picosulfate, magnesium oxide, and anhydrous citric acid product in 16 healthy subjects, the mean ± SD maximum plasma concentration (Cmax) for picosulfate of 2.3 ± 1.4 ng/mL was reached at 2 hours. After administration of two doses separated by 6 hours, the mean ± SD plasma Cmax for picosulfate of 3.2 ± 2.6 ng/mL was reached at approximately 7 hours after the first dose administration. In the same study, the uncorrected plasma magnesium concentration reached a Cmax of approximately 1.9 mEq/L at 10 hours after the first dose administration, which represents an approximately 20% increase from baseline.

In patients scheduled to have an elective colonoscopy who received the Split-Dose dosage regimen of CLENPIQ, the mean ± SD plasma concentration for picosulfate was 1.05 ± 0.83 ng/mL at 15 minutes pre-second dose, 2.98 ± 1.27 ng/mL at 1-2 hours post-second dose, and 1.81 ± 0.86 ng/mL at 3-6 hours post-second dose.

Metabolism and Elimination

Metabolism and Excretion

Plasma concentrations of the free BHPM were below the lower limit of quantification (0.1 ng/mL) in 13 out of 16 subjects studied. The fraction of the sodium picosulfate dose excreted unchanged in urine was 0.1%. In urine, the majority of excreted BHPM was in the glucuronide-conjugated form. The terminal half-life of sodium picosulfate was 7.4 hours.

Use in Specific Populations

Pediatric Patients

Pharmacokinetics of picosulfate was studied in pediatric patients aged from 9 to 16 years old. The half-life of picosulfate was 7 hours. The picosulfate reached the mean ± SD Cmax of 3.5 ± 2.1 ng/mL at approximately 6 to 7 hours. The baseline uncorrected mean serum magnesium concentration was 2.02 mEq/L at 10 hours after the first dose of sodium picosulfate, magnesium oxide, and anhydrous citric acid and ranged from 1.7 to 2.46 mEq/L.

Drug Interaction Studies

In an in vitro study using human liver microsomes, sodium picosulfate did not inhibit the major CYP enzymes (CYP 1A2, 2B6, 2C8, 2C9, 2C19, 2D6, and 3A4/5) evaluated. Based on an in vitro study using freshly isolated hepatocyte culture, sodium picosulfate is not an inducer of CYP1A2, CYP2B6, or CYP3A4/5.

13 NONCLINICAL TOXICOLOGY

13.1 Carcinogenesis, Mutagenesis, Impairment of Fertility

Long-term studies in animals to evaluate carcinogenic potential or studies to evaluate mutagenic potential have not been performed with CLENPIQ.

Sodium picosulfate was not mutagenic in the Ames test, the mouse lymphoma assay, and the mouse bone marrow micronucleus test.

In an oral fertility study in rats, sodium picosulfate, magnesium oxide, and anhydrous citric acid did not cause any significant adverse effect on male or female fertility parameters up to a maximum dose of 2000 mg/kg twice daily (about 1.2 times the recommended human dose based on body surface area).

14 CLINICAL STUDIES

Adults

Clinical Study with CLENPIQ – Study 1

The colon-cleansing efficacy of CLENPIQ was evaluated in a randomized, investigator-blinded, active-controlled, multicenter non-inferiority trial in the US and Canada in adult patients scheduled to have an elective colonoscopy (NCT03017235). Patients were randomized to CLENPIQ or another oral sodium picosulfate, magnesium oxide, and anhydrous citric acid product. Both products were administered by the "Split-Dose" (evening before and day of) dosing, where the first dose was taken the evening before the colonoscopy (between 5:00 and 9:00 PM), followed by at least five (5) 8-ounce glasses of clear liquid, and the second dose was taken the morning of the colonoscopy (at least 5 hours prior to but no more than 9 hours prior to colonoscopy), followed by at least four (4) 8-ounce glasses of clear liquid. Patients in both treatment groups were limited to a clear liquid diet on the day before the procedure (24 hours before).

A total of 901 adult patients were included in the primary efficacy analysis. Patients ranged in age from 20 to 80 years (mean age 57 years); 56% were female and 44% male. Self-identified race was approximately distributed as follows: 85% White, 10% Black, 2% Asian, and 3% other. Approximately 15% of patients self-identified their ethnicity as Hispanic or Latino.

The primary efficacy endpoint was the proportion of patients with successful overall colon cleansing, as assessed by blinded colonoscopists using the Modified Aronchick Scale. The Modified Aronchick Scale is a validated tool used to assess overall colon cleansing prior to suctioning or cleaning. Successful colon cleansing was defined as bowel preparations with >90% of the mucosa seen and mostly liquid stool that were graded excellent (minimal suctioning needed for adequate visualization) or good (significant suctioning needed for adequate visualization) by the colonoscopist.

In the trial, CLENPIQ was non-inferior and also met the pre-specified criteria for superiority to the comparator for overall colon cleansing. Efficacy results are provided in Table 4.

Table 4: Proportion of Patients with Successful Colon Cleansing According to the Modified Aronchick Scale in Study 1 Using the Split-Dose Regimen
CLENPIQ | Sodium picosulfate, magnesium oxide, and anhydrous citric acid [Powder for reconstitution] | Difference between treatment groups [Difference and 95% CI are based on stratified difference in proportions, where the stratification weight is based on Cochran-Mantel-Haenszel weight.]
% (n/N) | % (n/N) | Difference | 95% CI
87.7% (393/448) | 81.5% (369/453) | 6.3% | (1.8%, 10.9%) [Non-inferior and superior to sodium picosulfate, magnesium oxide, and anhydrous citric acid]

Clinical Study of Another Oral Sodium Picosulfate, Magnesium Oxide and Anhydrous Citric Acid Product – Study 2

The colon cleansing efficacy of another oral sodium picosulfate, magnesium oxide, and anhydrous citric acid product was evaluated in a randomized, investigator-blinded, active-controlled, multicenter US non-inferiority trial in adult patients scheduled to have an elective colonoscopy (NCT01073930).

Patients were randomized to sodium picosulfate, magnesium oxide, and anhydrous citric acid group or polyethylene glycol plus electrolytes (PEG + E) and bisacodyl.

- Sodium picosulfate, magnesium oxide, and anhydrous citric acid was given by "Split-Dose" (evening before and day of) dosing, where the first dose was taken the evening before the colonoscopy (between 5:00 and 9:00 PM), followed by five (5) 8-ounce glasses of clear liquid, and the second dose was taken the morning of the colonoscopy (at least 5 hours prior to but no more than 9 hours prior to colonoscopy), followed by three (3) 8-ounce glasses of clear liquid.
- The comparator was given as two liters of polyethylene glycol plus electrolytes solution (PEG + E) and two 5-mg bisacodyl tablets, administered the day before the procedure.

All patients in both treatment groups were limited to a clear liquid diet on the day before the procedure (24 hours before).

A total of 601 adult patients were included in the primary efficacy analysis. Patients ranged in age from 18 to 80 years (mean age 55 years); 59% were female and 41% male. Self-identified race was distributed as follows: 88% White, 10% Black, and less than 2% other. Of these, 2% self-identified their ethnicity as Hispanic or Latino.

The primary efficacy endpoint was the proportion of patients with successful colon cleansing, as assessed by blinded colonoscopists using the Aronchick Scale. The Aronchick scale is a tool used to assess overall colon cleansing. Successful colon cleansing was defined as bowel preparations with >90% of the mucosa seen and mostly liquid stool that were graded excellent (minimal suctioning needed for adequate visualization) or good (significant suctioning needed for adequate visualization) by the colonoscopist.

Sodium picosulfate, magnesium oxide, and anhydrous citric acid was non-inferior to the comparator. In addition, sodium picosulfate, magnesium oxide, and anhydrous citric acid met the pre-specified criteria for superiority to the comparator for colon cleansing. Efficacy results are provided in Table 5.

Table 5: Proportion of Patients with Successful Colon Cleansing in Study 2
Sodium picosulfate, magnesium oxide, and anhydrous citric acid | 2 L PEG+E [2 L PEG + E = two liters polyethylene glycol plus electrolytes solution.] with 2 × 5-mg bisacodyl tablets | Difference between treatment groups
% (n/N) | % (n/N) | Difference | 95% CI
84% (256/304) | 74% (221/297) | 10% | (3.4%, 16.2%) [Non-inferior and superior to 2 L PEG+E with 2 × 5-mg bisacodyl tablets]

Pediatric Patients 9 Years of Age and Older

The safety and efficacy of CLENPIQ in pediatric patients 9 years of age and older has been established based on another oral product of sodium picosulfate, magnesium oxide and anhydrous citric acid provided in powder packets for reconstitution (NCT01928862).

Sodium picosulfate, magnesium oxide, and anhydrous citric acid was evaluated for colon cleansing in a randomized, assessor-blind, multicenter, dose-ranging, active-controlled study in 78 pediatric patients 9 years to 16 years of age. The majority of patients were female (68%), white (91%), and of non-Hispanic or non-Latino ethnicity (95%). The mean age was 12 years of age. All 78 patients were included in the primary efficacy analysis.

Patients aged 9 years to 12 years were randomized into 3 arms (1:1:1):

- Sodium picosulfate, magnesium oxide, and anhydrous citric acid one-half packet per dose administered as two doses
- Sodium picosulfate, magnesium oxide, and anhydrous citric acid one packet per dose administered as two doses
- Comparator (oral PEG-based solution per local standard of care).

Patients aged 13 years to 16 years were randomized into 2 arms (1:1):

- Sodium picosulfate, magnesium oxide, and anhydrous citric acid one packet per dose administered as two doses
- Comparator (oral PEG-based solution per local standard of care)

Patients randomized to sodium picosulfate, magnesium oxide, and anhydrous citric acid had two options for dosing, as determined by the investigator. The "Split-Dose" regimen was the preferred method and the "Day-Before" regimen was the alternative method if the "Split-Dose" was not appropriate.

"Split-Dose" Regimen: (evening before and day of) dosing, where the first dose was taken the evening before the colonoscopy (between 5:00 and 9:00 PM), followed by five (5) 8-ounce glasses of clear liquid, and the second dose was taken the morning of the colonoscopy (at least 5 hours prior to but no more than 9 hours prior to colonoscopy), followed by three (3) 8-ounce glasses of clear liquid.

"Day-Before" Regimen: (afternoon/evening before only) dosing, where both doses were taken separately on the day before the colonoscopy, with the first dose taken in the afternoon (between 4:00 and 6:00 PM), followed by five (5) 8-ounce glasses of clear liquid, and the second dose taken in the late evening (approximately 6 hours later, between 10:00 PM and 12:00 AM), followed by three (3) 8-ounce glasses of clear liquid.

All patients randomized to sodium picosulfate, magnesium oxide, and anhydrous citric acid was limited to a clear liquid diet on the day before the procedure. Those who received the comparator were given dietary instructions per the trial site's standard of care.

The primary efficacy endpoint was the proportion of patients with successful colon cleansing as defined as a rating of either "Excellent" (> 90% of mucosa seen, mostly liquid stool, minimal suctioning needed for adequate visualization) or "Good" (> 90% of mucosa seen, mostly liquid stool, significant suctioning needed for adequate visualization) using the Aronchick scale, as assessed by blinded colonoscopists.

The sodium picosulfate, magnesium oxide, and anhydrous citric acid regimen of one-half packet per dose administered as two doses did not demonstrate comparable efficacy to the comparator, PEG, in patients 9 to 12 years of age and is not a CLENPIQ recommended dosage regimen [see Dosage and Administration (2)].

The sodium picosulfate, magnesium oxide, and anhydrous citric acid regimen of one packet per dose administered as two doses demonstrated successful colon cleansing in both the 9 to 12 year age group and the 13 to 16 year age group. The efficacy rates were similar to those observed in the PEG groups, as shown in Table 6.

Table 6. Proportion of Patients 9 to 16 Years of Age with Successful Colon Cleansing [Successful colon cleansing as defined by "Excellent" or "Good" on the Aronchick scale]
 | Sodium Picosulfate, Magnesium Oxide, and Anhydrous Citric Acid, One Packet Administered as Two Doses either as Split Dose or Day Before Regimen [Of the 32 patients, 9 received the Split Dose Regimen and 23 the Day Before Regimen] |  | PEG Comparator [Oral PEG-based preparation was used in the study as per standard of care]
 | % (n/N) | 95% CI | % (n/N) | 95% CI
Age 9-12 | 88% (14/16) | (62, 98) | 81% (13/16) | (54, 96)
Age 13-16 | 81% (13/16) | (54, 96) | 86% (12/14) | (57, 98)

16 HOW SUPPLIED/STORAGE AND HANDLING

How Supplied

CLENPIQ is supplied in a carton containing two bottles, each holding 175 mL of cranberry-flavored, colorless to slightly yellow, clear oral solution with possible presence of visible particles. Each bottle contains 10 mg sodium picosulfate, 3.5 g magnesium oxide, and 12 g anhydrous citric acid. An eight-ounce cup for measuring liquids for hydration is also supplied.

CLENPIQ Cranberry flavor: NDC# 55566-6800-1.

Storage

Store CLENPIQ at 25°C (77°F). Excursions permitted at 15°C to 30°C (59°F to 86°F). [See USP Controlled Room Temperature]. Do not refrigerate or freeze.

17 PATIENT COUNSELING INFORMATION

Advise the patient to read the FDA-approved patient labeling (Medication Guide and Instructions for Use).

Instruct patients:

- CLENPIQ is ready to drink. It is a clear solution with possible presence of visible particles and it does not need to be diluted prior to administration. One bottle of CLENPIQ is equivalent to one dose.
- Two doses of CLENPIQ are required for a complete preparation for colonoscopy as a Split-Dose regimen. See Instructions for Use.
- Follow the directions in the Instructions for Use, for the Split-Dose regimen, as prescribed.
- Consume five or more 8-ounce cups of clear liquids after the first dose and four or more 8-ounce cups of clear liquids after the second dose [see Dosage and Administration (2.2)].
- Consume a variety of clear liquids after each dose of CLENPIQ. Ensure inclusion of balanced electrolyte solution, along with other clear liquids [see Dosage and Administration (2.1), Warnings and Precautions (5.1, 5.5)].
- Consume only clear liquids (no solid food) on the day before colonoscopy and until after the colonoscopy.
- Do not eat solid food or dairy and do not drink anything colored red or purple.
- Do not drink alcohol.
- Do not take other laxatives while taking CLENPIQ.
- Administer oral medications at least one hour before starting each dose of CLENPIQ.
- If taking tetracycline or fluoroquinolone antibiotics, iron, digoxin, chlorpromazine, or penicillamine, take these medications at least 2 hours before and not less than 6 hours after administration of CLENPIQ.
- Delay the second dose of CLENPIQ, if severe bloating, distention, or abdominal pain occurs following the first dose until the symptoms resolve.
- Tell their healthcare provider if they have a history of fainting [see Warnings and Precautions (5.5)].
- Contact their healthcare provider if they develop significant vomiting or signs of dehydration during or after taking CLENPIQ or if they experience confusion, delirium, dizziness, lightheadedness, fainting, loss of consciousness, or seizures [see Warnings and Precautions (5.1, 5.2, 5.4, 5.5)].

Manufactured by:

ASM Aerosol-Service AG
Industriestrasse 11, CH - 4313 Möhlin
Switzerland

Manufactured for:

Ferring Pharmaceuticals Inc.
Parsippany, N.J. 07054

Rev. 10/2024

MEDICATION GUIDE
CLENPIQ® (CLEN-pik)
(sodium picosulfate, magnesium oxide, and anhydrous citric acid)
oral solution

Read and understand these Medication Guide instructions at least 2 days before your colonoscopy and again before you start taking CLENPIQ.

What is the most important information I should know about CLENPIQ?

CLENPIQ and other bowel preparations can cause serious side effects, including:

- Serious loss of body fluid (dehydration) and changes in blood salts (electrolytes) in your blood. These changes can cause:
  - abnormal heartbeats that can cause death.
  - seizures. This can happen even if you have never had a seizure.
  - kidney problems.
  - fainting.

Your chance of having fluid loss and changes in blood salts with CLENPIQ is higher if you:

- have heart problems
- have kidney problems
- take water pills or non-steroidal anti-inflammatory drugs (NSAIDS)

Tell your healthcare provider right away if you have any of these symptoms of a loss of too much body fluid (dehydration) while taking CLENPIQ:

- vomiting
- urinating less often than normal

- dizziness
- headache

See "What are the possible side effects of CLENPIQ?" for more information about side effects.

What is CLENPIQ?

CLENPIQ is a prescription medicine used by adults and children 9 years of age and older to clean the colon before a colonoscopy. CLENPIQ cleans your colon by causing you to have diarrhea. Cleaning your colon helps your healthcare provider see the inside of your colon more clearly during your colonoscopy.

It is not known if CLENPIQ is safe and effective in children under 9 years of age.

Do not take CLENPIQ if your healthcare provider has told you that you have:

- serious kidney problems.
- a blockage in your intestine (bowel obstruction).
- an opening in the wall of your stomach or intestines (bowel perforation).
- a very dilated intestine (toxic megacolon).
- problems with the emptying of food and fluid from your stomach (gastric retention).
- an allergy to any of the ingredients in CLENPIQ. See the end of this leaflet for a complete list of ingredients in CLENPIQ.

Before taking CLENPIQ, tell your healthcare provider about all of your medical conditions, including if you:

- have problems with serious loss of body fluid (dehydration) and changes in blood salts (electrolytes).
- have a history of seizures or take medicines for seizures.
- history of fainting.
- are withdrawing from drinking alcohol or from taking benzodiazepines.
- have low blood salt (sodium) level.
- have kidney problems or take medicines for kidney problems.
- have heart problems.
- have stomach or bowel problems including ulcerative colitis.
- have problems with swallowing or gastric reflux.
- are pregnant. It is not known if CLENPIQ will harm your unborn baby. Talk to your provider if you are pregnant.
- are breastfeeding or plan to breastfeed. It is not known if CLENPIQ passes into your breast milk. You and your healthcare provider should decide if you will take CLENPIQ while breastfeeding.

Tell your healthcare provider about all the medicines you take, including prescription and non-prescription medicines, vitamins, and herbal supplements.

CLENPIQ may affect how other medicines work. Medicines taken by mouth may not be absorbed properly when taken within 1 hour before the start of CLENPIQ.

Especially tell your healthcare provider if you take:

- medicines for blood pressure or heart problems.
- medicines for kidney problems.
- medicines for seizures.
- water pills (diuretics).
- nonsteroidal anti-inflammatory medicines (pain medicines).
- medicines for depression or mental health problems.
- laxatives. Do not take other laxatives while taking CLENPIQ.

The following medicines should be taken at least 2 hours before starting CLENPIQ and not less than 6 hours after taking CLENPIQ:

- tetracycline
- fluoroquinolone antibiotics
- iron
- digoxin (Lanoxin)
- chlorpromazine
- penicillamine (Cuprimine, Depen)

Ask your healthcare provider or pharmacist for a list of these medicines if you are not sure if you are taking the medicines listed above.

Know the medicines you take. Keep a list of them to show your healthcare provider and pharmacist when you get a new medicine.

How should I take CLENPIQ?

See the Instructions for Use for dosing instructions. You must read, understand, and follow these instructions to take CLENPIQ the right way.

- Take CLENPIQ exactly as your healthcare provider tells you to take it.
- CLENPIQ comes ready to drink and does not need to be mixed with anything else before you take your dose of medicine.
- CLENPIQ is a clear liquid that may have particles.
- 1 bottle of CLENPIQ equals 1 dose. Two separate doses of CLENPIQ are required for complete colonoscopy preparation.
- CLENPIQ is taken using the Split-Dose method. See the instructions for use for more information.
- All people taking CLENPIQ should follow these general instructions starting 1 day before your colonoscopy:
  - only drink clear liquids all day and the next day until 2 hours before your colonoscopy. Stop drinking all fluids at least 2 hours before the colonoscopy.
  - after taking CLENPIQ if you have any bloating or feeling like your stomach is upset, wait to take your second dose until your stomach feels better.

- If you need to take any other medicines by mouth (oral), take those medicines at least 1 hour before starting each dose of CLENPIQ.
- While taking CLENPIQ, do not:
  - take any other laxatives.
  - eat solid foods, dairy such as milk, or alcohol while taking CLENPIQ and until after your colonoscopy.
  - eat or drink anything colored red or purple.

Contact your healthcare provider right away if after taking CLENPIQ you have severe vomiting, signs of dehydration, changes in consciousness such as feeling confused, delirious or fainting (loss of consciousness) or seizures after taking CLENPIQ.

What are the possible side effects of CLENPIQ?

CLENPIQ can cause serious side effects, including:

See "What is the most important information I should know about CLENPIQ"?

- Changes in certain blood tests. Your healthcare provider may do blood tests after you take CLENPIQ to check your blood for changes.
- Tell your healthcare provider if you have any symptoms of too much fluid loss, including:

- vomiting
- stomach area (abdominal) cramping
- seizures

- nausea
- urinate less than usual
- fainting

- bloating
- trouble drinking clear liquids
- heart problems

- dizziness
- troubles swallowing

- Ulcers of the bowel or bowel problems (ischemic colitis). Tell your healthcare provider right away if you have severe stomach-area (abdominal) pain or rectal bleeding.

The most common side effects of CLENPIQ in adults include:

- nausea
- headache

- high magnesium levels in your blood
- stomach area (abdominal) pain

- dehydration or dizziness

The most common side effects of CLENPIQ in children 9 to 16 years of age include:

- nausea

- vomiting

- stomach area (abdominal) pain

These are not all the possible side effects of CLENPIQ.

Call your doctor for medical advice about side effects. You may report side effects to FDA at 1-800-FDA-1088.

How should I store CLENPIQ?

- Store CLENPIQ at room temperature, between 68° to 77°F (20° to 25°C).
- Do not put CLENPIQ in the refrigerator or freezer.

Keep CLENPIQ and all medicines out of the reach of children.

General information about the safe and effective use of CLENPIQ.

Medicines are sometimes prescribed for purposes other than those listed in a Medication Guide. Do not use CLENPIQ for a condition for which it was not prescribed. Do not give CLENPIQ to other people, even if they have the same symptoms that you have. It may harm them. You can ask your pharmacist or healthcare provider for information about CLENPIQ that is written for health professionals.

What are the ingredients in CLENPIQ?

CLENPIQ comes in a carton containing 2 bottles, along with an 8-ounce cup for measuring fluids for hydration.

Each bottle contains:

Active ingredients: sodium picosulfate, magnesium oxide, and anhydrous citric acid

Inactive ingredients:
acesulfame potassium, cranberry flavor, disodium edetate, malic acid, sodium benzoate, sodium hydroxide, sodium metabisulfite, sucralose, and water. The cranberry flavor contains glyceryl triacetate (triacetin), maltodextrin, and sodium octenyl succinated starch.

Manufactured for: Ferring Pharmaceuticals Inc.
Parsippany, NJ 07054, USA

For more information, go to www.CLENPIQ.com or call 1-888-337-7464.

This Medication Guide has been approved by the U.S. Food and Drug Administration

Revised: 08/2023

Instructions for Use CLENPIQ® (CLEN-pik) (sodium picosulfate, magnesium oxide, and anhydrous citric acid) oral solution

NOTE: Do not refrigerate or freeze CLENPIQ. CLENPIQ is ready to drink and does not need to be mixed with anything. CLENPIQ is a clear liquid that may have particles.

READ BEFORE Taking CLENPIQ

If you have questions before you start CLENPIQ, talk to your healthcare provider.

Take CLENPIQ using the Split-Dose method. This means you will take 2 separate doses. Each bottle is 1 dose and has the same ingredients. You can drink either bottle first.

- Drink the first bottle the evening before your colonoscopy.
- Drink the second bottle the morning of your colonoscopy.

Start a clear-liquid diet the day before your colonoscopy. Do not eat any solid foods. Drink a variety of clear liquids. Clear liquids should include balanced electrolyte solution such as sports drinks (see Table 1).

- Drink only clear liquids all day the day before your colonoscopy.
- Drink only clear liquids the next day until 2 hours before your colonoscopy.
- Stop drinking all liquids at least 2 hours before your colonoscopy.

You must drink enough clear liquids to keep hydrated.

- Drink FIVE or more 8-ounce cups of clear liquids after the first dose.
- Drink FOUR or more 8-ounce cups of clear liquids after the second dose.

IMPORTANT: You can drink the clear liquids in Table 1.

TABLE 1: List of liquids for the clear-liquid diet

- Water, plain or flavored. Do not drink only water.
- Black coffee or tea (no milk, cream, soy, or nondairy creamer)
- Sports drinks (not red or purple)
- Plain jello (not red or purple)
- Clear broth or bouillon
- Clear juices without pulp (such as apple juice or white grape juice)
- Ginger ale and other sodas (not red or purple)
- Frozen juice bars (not red or purple)

IMPORTANT: Do NOT eat or drink the items in Table 2 starting from the day before your colonoscopy.

TABLE 2: List of foods and drinks to avoid while you are on the clear-liquid diet

- no solid foods
- no alcohol
- no dairy or non-dairy types of milk or cream
- no soy milk or drinks
- no juices with pulp
- no red or purple drinks
- no red or purple jello
- no other liquids that you cannot see through

SPLIT-DOSE INSTRUCTIONS

DOSE 1

In the evening the day before your colonoscopy (sometime between 5:00 PM to 9:00 PM)

- Place the first bottle on a flat surface. Push down on the cap while twisting to the left (counterclockwise).
- Drink the entire first bottle of CLENPIQ. Drink CLENPIQ right from the bottle.
- Use the cup provided to drink five or more 8-ounce (oz) cups of clear liquids over the next 5 hours.

IMPORTANT: See Table 1 for a list of clear liquids you can drink.

If you have any bloating or upset stomach after drinking CLENPIQ, wait until your stomach feels better before taking your second dose.

DOSE 2

In the morning of your colonoscopy (about 5 hours before your colonoscopy)

- Place the second bottle on a flat surface. Push down on the cap while twisting to the left (counterclockwise).
- Drink the entire second bottle of CLENPIQ. Drink CLENPIQ right from the bottle.
- Use the cup provided to drink four or more 8 ounce (oz) cups of clear liquids. You can continue to drink clear liquids up to 2 hours before the colonoscopy.

Do not eat solid food. Drink only clear liquids. Do not drink only plain water (see Table 1).

IMPORTANT: See Table 1 for a list of clear liquids you can drink.

Stop drinking clear liquids 2 hours before your colonoscopy, or as advised by your healthcare provider.

This Instructions for Use has been approved by the U.S. Food and Drug Administration.

Ferring Pharmaceuticals Inc.
Parsippany, NJ 07054, USA
Revised 08/2023
2009010037

PRINCIPAL DISPLAY PANEL - 175 mL Bottle Carton

Cranberry
Flavor
NDC 55566-6800-1

CLENPIQ®

(sodium picosulfate, magnesium oxide,
and anhydrous citric acid) Oral Solution

10 mg/3.5 g/12 g per 175 mL bottle

CLENPIQ® is a ready-to-drink
oral solution that doesn't need to be diluted.

Read the enclosed Instructions for Use and Medication Guide
AT LEAST 2 DAYS BEFORE your colonoscopy
and again right before taking CLENPIQ®.

Contains two (2) 175 mL bottles

Do not refrigerate or freeze.

Rx only

FERRING
PHARMACEUTICALS